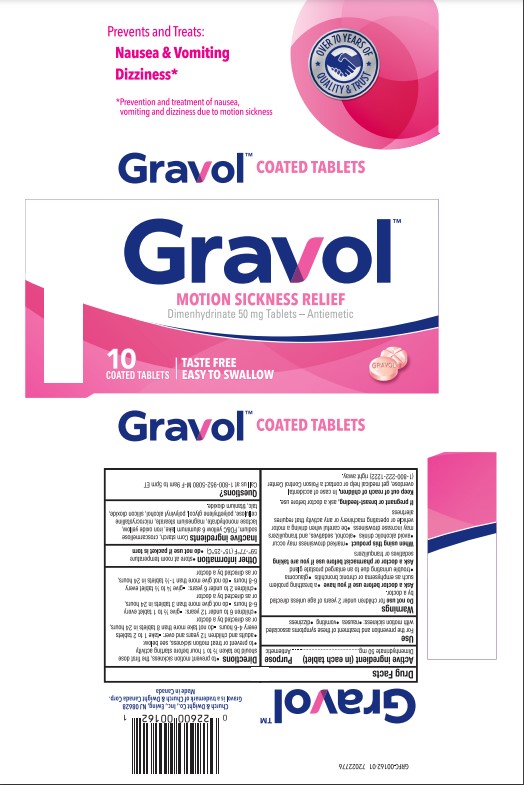 DRUG LABEL: Gravol
NDC: 10237-941 | Form: TABLET, COATED
Manufacturer: Church & Dwight Co., Inc.
Category: otc | Type: HUMAN OTC DRUG LABEL
Date: 20220303

ACTIVE INGREDIENTS: DIMENHYDRINATE 50 mg/1 1
INACTIVE INGREDIENTS: FERRIC OXIDE YELLOW; MAGNESIUM STEARATE; SILICON DIOXIDE; TALC; POLYETHYLENE GLYCOL, UNSPECIFIED; POLYVINYL ALCOHOL, UNSPECIFIED; TITANIUM DIOXIDE; CROSCARMELLOSE; STARCH, CORN; LACTOSE MONOHYDRATE; MICROCRYSTALLINE CELLULOSE; FD&C YELLOW NO. 6

Gravol™ Motion Sickness Relief - Coated Tablets

Active ingredient (in each tablet)

Dimenhydrinate 50 mg

Purpose

Antiemetic

Use

For prevention and treatment of these symptoms associated with motion sickness:

- nausea
- vomiting
- dizziness

Warnings

Do not use

for children under 2 years of age unless directed by a doctor.

Ask a doctor before use if you have

- a breathing problem such as emphysema or chronic bronchitis
- glaucoma
- trouble urinating due to an enlarged prostate gland

Ask a doctor or pharmacist before use if you are taking

sedatives or tranquilizers

When using this product

- marked drowsiness may occur
- avoid alcoholic drinks
- alcohol, sedatives, and tranquilizers may increase dizziness
- be careful when driving a motor vehicle or operating machinery or any activity that requires alertness

If pregnant or breast-feeding,

ask a doctor before use.

Keep out of reach of children.

In case of accidental overdose, get medical help or contact a Poison Control Center (1-800-222-1222) right away.

Directions

- to prevent motion sickness, the first dose should be taken ½ to 1 hour before starting activity
- to prevent or treat motion sickness, see below:

adults and children 12 years and over: | - take 1 to 2 tablets every 4-6 hours - do not take more than 8 tablets in 24 hours, or as directed by a doctor
children 6 to under 12 years: | - give 1/2 to 1 tablet every 6-8 hours - do not give more than 3 tablets in 24 hours, or as directed by a doctor
children 2 to under 6 years: | - give 1/4 to 1/2 tablet every 6-8 hours - do not give more than 1-1/2 tablets in 24 hours, or as directed by a doctor

Other information

- store at room temperature 59º-77ºF (15º-25ºC)
- do not use if packet is torn

Inactive ingredients

Corn starch, croscarmellose sodium, FD&C yellow 6 aluminum lake, iron oxide yellow, lactose monohydrate, magnesium stearate, microcrystalline cellulose, polyethylene glycol, polyvinyl alcohol, silicon dioxide, talc, titanium dioxide

Questions or comments?

1-800-952-5080 M-F 9am to 5pm ET

PRINCIPAL DISPLAY PANEL

OVER 70 YEARS OF

QUALITY & TRUST†

Prevents and Treats:

Nausea & Vomiting

Dizziness*

*Prevention and treatment of nausea,

vomiting and dizziness due to motion sickness

Gravol™ COATED TABLETS

Gravol™

MOTION SICKNESS RELIEF

Dimenhydrinate 50 mg Tablets - Antiemetic

10

COATED TABLETS

TASTE FREE

EASY TO SWALLOW